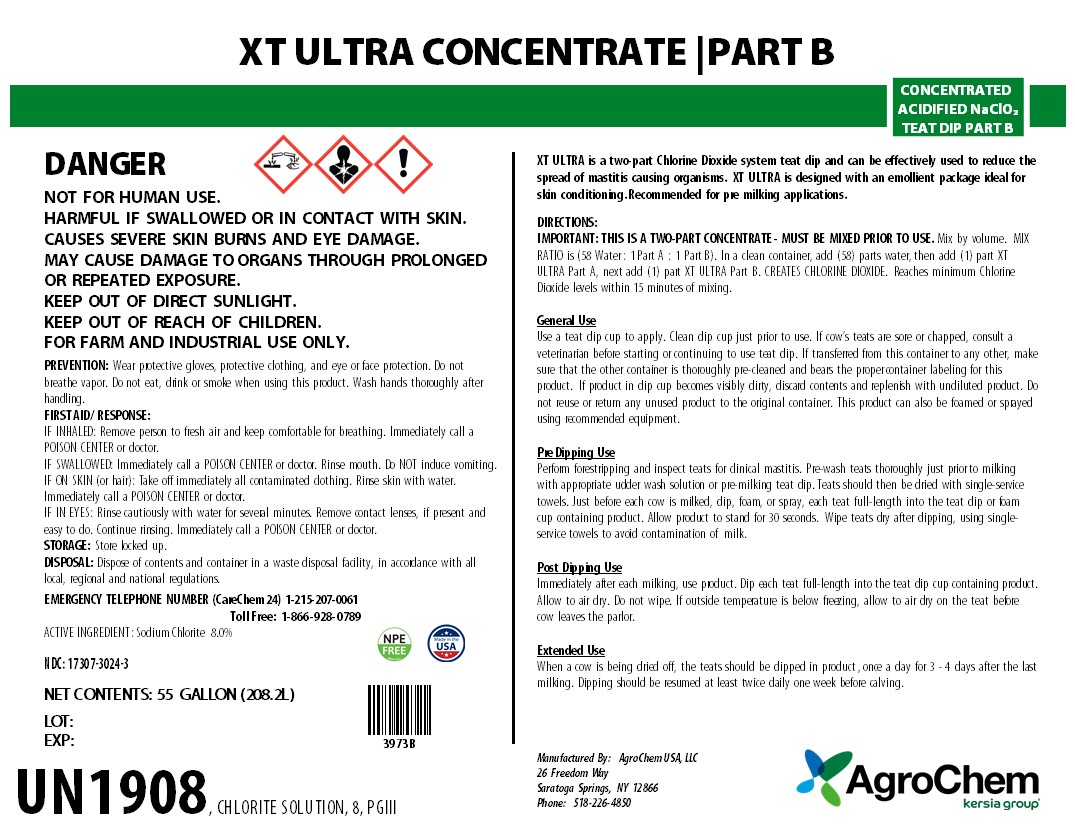 DRUG LABEL: XT ULTRA CONC. PART B
NDC: 17307-3024 | Form: SOLUTION
Manufacturer: AgroChem USA, LLC
Category: animal | Type: OTC ANIMAL DRUG LABEL
Date: 20240719

ACTIVE INGREDIENTS: SODIUM CHLORITE 0.27 kg/1 kg

XT ULTRA CONC. PART B

XT ULTRA CONC. PART B

CONCENTRATED ACIDIFIED NaClO2 TEAT DIP PART B

WARNINGS AND PRECAUTIONS

DANGER

KEEP OUT OF REACH OF CHILDREN

WARNINGS AND PRECAUTIONS

NOT FOR HUMAN USE.

HARMFUL IF SWALLOWED OR IN CONTACT WITH SKIN.

CAUSES SEVERE SKIN BURNS AND EYE DAMAGE.

MAY CAUSE DAMAGE TO ORGANS THROUGH PROLONGED OR REPEATED EXPOSURE.

KEEP OUT OF DIRECT SUNLIGHT.

FOR FARM AND INDUSTRIAL USE ONLY.

PREVENTION: Wear protective gloves, protective clothing, and eye or face protection. Do not breathe vapor. Do not eat, drink or smoke when using this product. Wash hands thoroughly after handling.

FIRST AID/ RESPONSE:

IF INHALED: Remove person to fresh air and keep comfortable for breathing. Immediately call a POISON CENTER or doctor.

IF SWALLOWED: Immediately call a POISON CENTER or doctor. Rinse mouth. Do NOT induce vomiting.

IF ON SKIN (or hair): Take off immediately all contaminated clothing. Rinse skin with water. Immediately call a POISON CENTER or doctor.

IF IN EYES: Rinse cautiously with water for several minutes. Remove contact lenses, if present and easy to do. Continue rinsing. Immediately call a POISON CENTER or doctor.

STORAGE: Store locked up.

DISPOSAL: Dispose of contents and container in a waste disposal facility, in accordance with all local, regional and national regulations.

EMERGENCY TELEPHONE NUMBER (CareChem 24) 1-215-207-0061

Toll Free: 1-866-928-0789

ACTIVE INGREDIENT : Sodium Chlorite 8.0%

NDC: 17307-3024-3

LOT:

EXP. DATE:

NET CONTENTS: 55 GALLON (208.2L)

XT ULTRA is a two-part Chlorine Dioxide system teat dip and can be effectively used to reduce the spread of mastitis causing organisms. XT ULTRA is designed with an emollient package ideal for skin conditioning. Recommended for pre milking applications.

General Use

Use a teat dip cup to apply. Clean dip cup just prior to use. If cow’s teats are sore or chapped, consult a veterinarian before starting or continuing to use teat dip. If transferred from this container to any other, make sure that the other container is thoroughly pre-cleaned and bears the proper container labeling for this product. If product in dip cup becomes visibly dirty, discard contents and replenish with undiluted product. Do not reuse or return any unused product to the original container. This product can also be foamed or sprayed using recommended equipment.

Pre Dipping Use

Perform forestripping and inspect teats for clinical mastitis. Pre-wash teats thoroughly just prior to milking with appropriate udder wash solution or pre-milking teat dip. Teats should then be dried with single-service towels. Just before each cow is milked, dip, foam, or spray, each teat full-length into the teat dip or foam cup containing product. Allow product to stand for 30 seconds. Wipe teats dry after dipping, using single-service towels to avoid contamination of milk.

Post Dipping Use

Immediately after each milking, use product. Dip each teat full-length into the teat dip cup containing product. Allow to air dry. Do not wipe. If outside temperature is below freezing, allow to air dry on the teat before cow leaves the parlor.

Extended Use

When a cow is being dried off, the teats should be dipped in product , once a day for 3 - 4 days after the last milking. Dipping should be resumed at least twice daily one week before calving.

Manufactured By:

AgroChem USA, LLC 26 Freedom Way • Saratoga Springs, NY 12866 • (518)226-4850